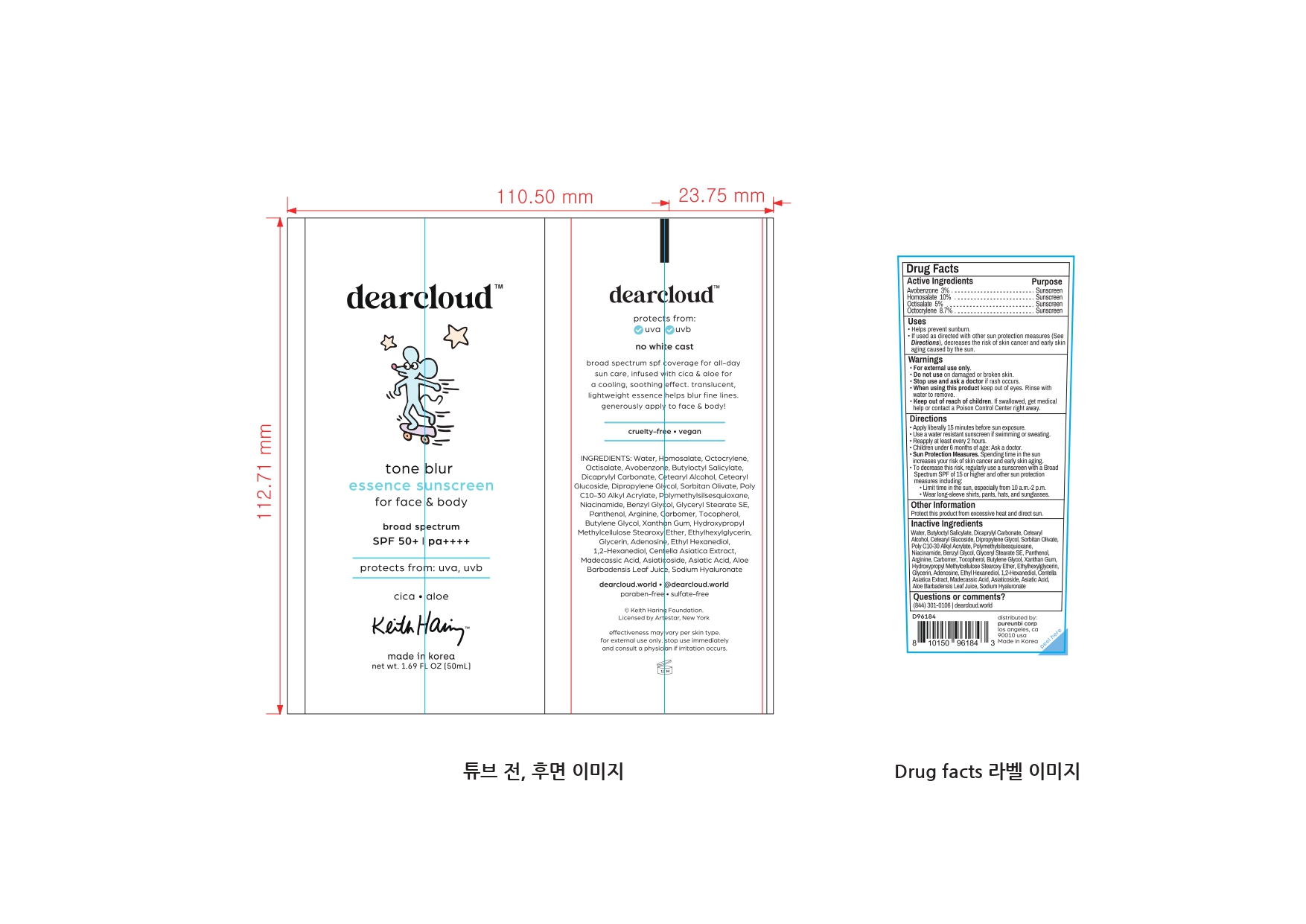 DRUG LABEL: Keith Haring Tone Blur Essence Sunscreen
NDC: 84326-324 | Form: CREAM
Manufacturer: RBGROUP Co., Ltd
Category: otc | Type: HUMAN OTC DRUG LABEL
Date: 20251021

ACTIVE INGREDIENTS: AVOBENZONE 1.5 g/50 mL; HOMOSALATE 5 g/50 mL; OCTOCRYLENE 4.35 g/50 mL; OCTISALATE 2.5 g/50 mL
INACTIVE INGREDIENTS: ETHYLENE GLYCOL MONOBENZYL ETHER; ARGININE; ETHYLHEXYLGLYCERIN; GLYCERIN; ETHOHEXADIOL; 1,2-HEXANEDIOL; ASIATICOSIDE; HYALURONATE SODIUM; CETEARYL GLUCOSIDE; DIPROPYLENE GLYCOL; PANTHENOL; MADECASSIC ACID; WATER; SORBITAN OLIVATE; POLYMETHYLSILSESQUIOXANE (4.5 MICRONS); NIACINAMIDE; GLYCERYL STEARATE SE; CARBOMER HOMOPOLYMER, UNSPECIFIED TYPE; ADENOSINE; CETOSTEARYL ALCOHOL; TOCOPHEROL; BUTYLOCTYL SALICYLATE; DICAPRYLYL CARBONATE; BEHENYL ACRYLATE POLYMER; BUTYLENE GLYCOL; XANTHAN GUM; CENTELLA ASIATICA TRITERPENOIDS; ASIATIC ACID; ALOE VERA LEAF

84326-324 Keith Haring Tone Blur Essence Sunscreen

ACTIVE INGREDIENT

Avobenzone 3.0%

Homosalate 10.0%

Octisalate 5.0%

Octocrylene 8.7%

PURPOSE

Sunscreen

INDICATIONS AND USAGE

● Helps prevent sunburn.

● If used as directed with other sun protection measures (See Directions), decreases the risk of skin cancer and early skin aging caused by the sun.

WARNINGS

For external use only

DO NOT USE

● on damaed skin or broken skin

WHEN USING

● Keep out of eyes. Rinse with water to remove.

STOP USE

and ask a doctor if rash occurs.

KEEP OUT OF REACH OF CHILDREN

If swallowed, get medical help or contact a Poison Control Center right away.

OTHER SAFETY INFORMATION

● Protect this product from excessive heat and direct sun.

Directions

● Apply liberally 15 minutes before sun exposure.

● Use a water resistant sunscreen if swimming or swating.

● Reapply at least every 2 hours.

● Children under 6 months of age: Ask a doctor.

● Sun Protection Measures Spending time in the sun increases your risk of skin cancer and early skin aging. To decrease this risk, regularly use a sunscreen other sun protection measures including: ● Limit time in the sun, especially from 10 a.m. - 2 p.m. ● Wear long-sleeve shirts, pants, hats, and sunglasses.

INACTIVE INGREDIENT

Water, Butyloctyl Salicylate, Dicaprylyl Carbonate, Cetearyl Alcohol, Cetearyl Glucoside, Dipropylene Glycol, Sorbitan Olivate, Poly C10-30 Alkyl Acrylate, Polymethylsilsesquioxane, Niacinamide, Benzyl Glycol, Glyceryl Stearate SE, Panthenol, Arginine, Carbomer, Tocopherol, Butylene Glycol, Xanthan Gum, Hydroxypropyl Methylcellulose Stearoxy Ether, Ethylhexylglycerin, Glycerin, Adenosine, Ethyl Hexanediol, 1,2-Hexanediol, Centella Asiatica Extract, Madecassic Acid, Asiaticoside, Asiatic Acid, Aloe Barbadensis Leaf Juice, Sodium Hyaluronate